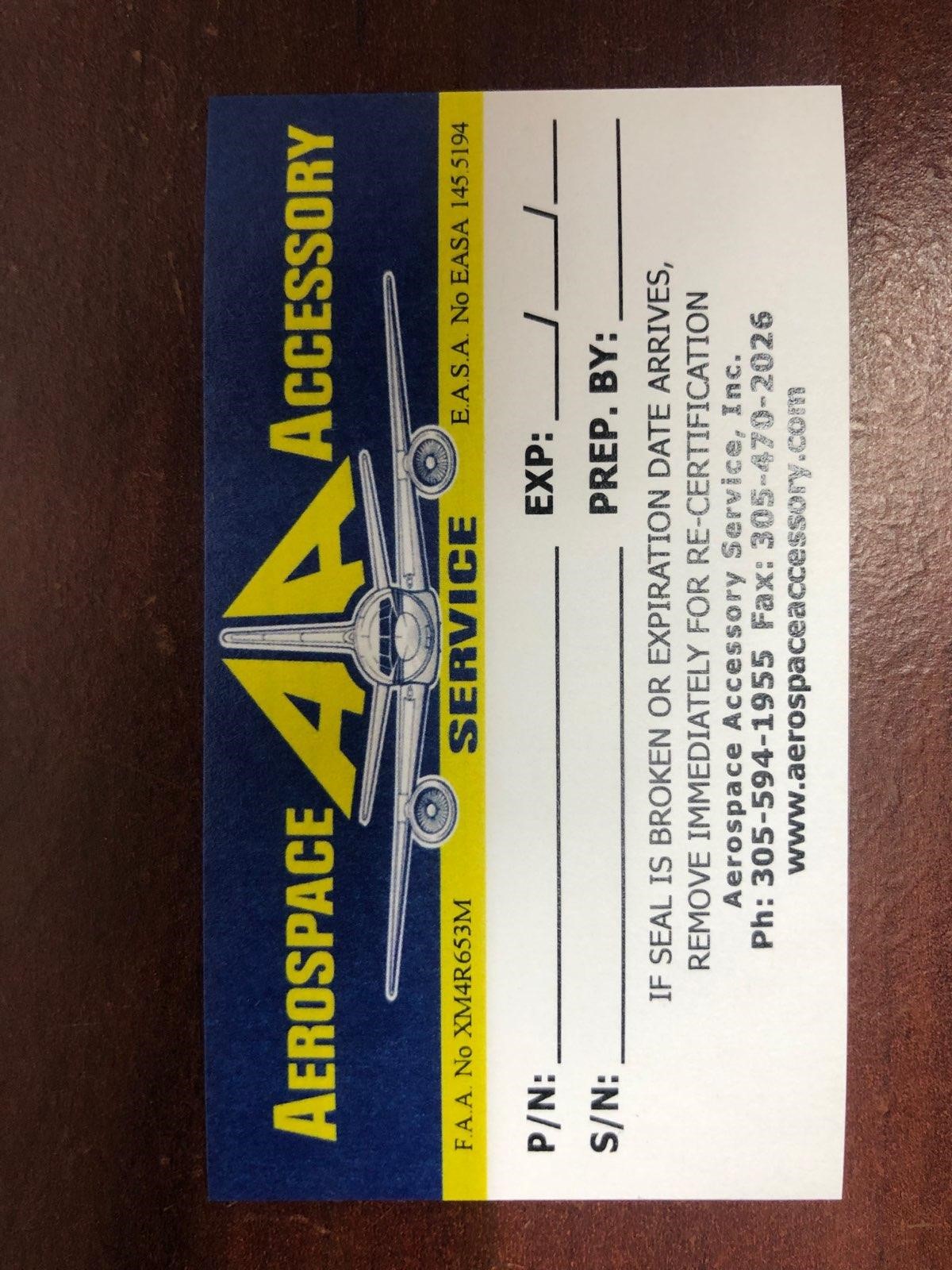 DRUG LABEL: Model AA-2012SK
NDC: 27860-006 | Form: KIT | Route: TOPICAL
Manufacturer: Aerospace Accessory Service, Inc
Category: other | Type: MEDICAL DEVICE
Date: 20210107

ACTIVE INGREDIENTS: BENZALKONIUM CHLORIDE 1.3 mg/1 mL
INACTIVE INGREDIENTS: WATER

Model AA-2012SK

Aerospace Accessory Service

P/N:

S/N:

EXP:

Prep. By: